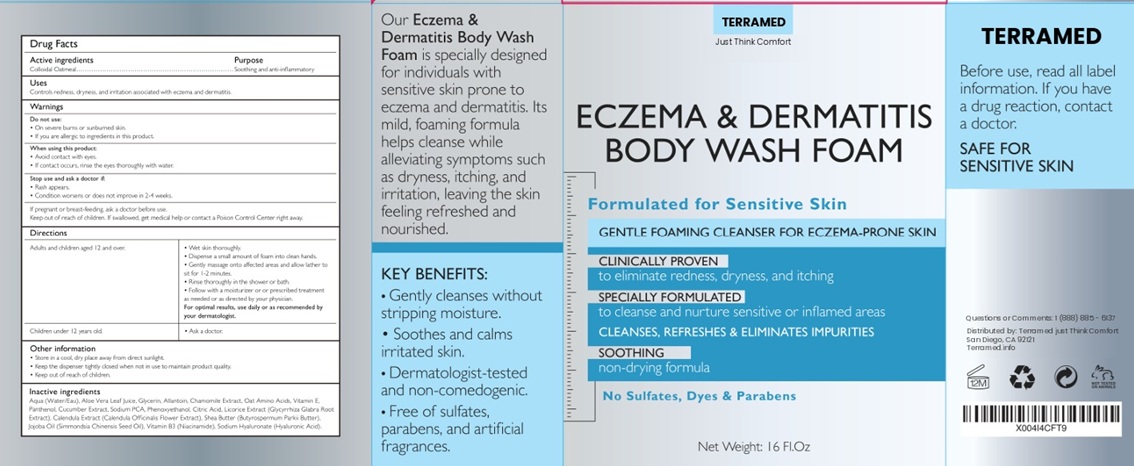 DRUG LABEL: Terramed Just Think Comfort Eczema and Dermatitis Body Wash Foam
NDC: 83004-024 | Form: AEROSOL, FOAM
Manufacturer: Rida LLC
Category: homeopathic | Type: HUMAN OTC DRUG LABEL
Date: 20250320

ACTIVE INGREDIENTS: OATMEAL 1 g/100 mL
INACTIVE INGREDIENTS: WATER; ALOE VERA LEAF; GLYCERIN; ALLANTOIN; CHAMOMILE; SODIUM PYRROLIDONE CARBOXYLATE; PANTHENOL; HYALURONATE SODIUM; BETAINE; CETOSTEARYL ALCOHOL; GLYCERETH-26; CETYL ALCOHOL; SODIUM CHLORIDE; JOJOBA OIL; CITRIC ACID MONOHYDRATE

Active Ingredient Purpose

Colloidal Oatmeal Soothing and anti-inflammatory

Uses

Controls redness, dryness, and irritation associated with eczema and dermatitis.

Warnings

Do not use:
• On severe burns or su nburned skin .
• If you are allergic to ingred ients in this product.

When using this product:
• Avoid contact with eyes
• If contact occurs, rinse the eyes thoroughly with water.

Stop use and ask a doctor if:
• Rash appears
• Condition worsens or does not improve in 2-4 weeks.

If pregnant or breast-feeding. ask a doctor before use
Keep o ut of reach of children. If swallowed, get medical help o r contact a Poison Control Center right away

Directions

Adults and children aged 12 and over. | • Wet skin thoro ughly.; • Dispense a small amount of foam into clean hands.; • Gently massage onto affected areas and allow lather to sit for 1-2 minutes; • Rinse thoroughly in the shower or bath.; • Follow with a moisturizer or o r prescribed treatment as needed or as directed by your physician.; For optimal results, use daily or as recommended by your dermatologist.
Children under 12 years old . | • Ask a doctor.

Other Information

- Store in a cool, dry place away from direct sunlight.
- Keep the dispenser tightly closed when not in use to maintain product quality.
- Keep out of reach of children.

Inactive ingredients

Aqua 0/Vat er/Eau), Aloe Vera Leaf Juice, Glycerin, Al lantoin, Chamomile Extract, Oat Amino Aci ds, Vitamin E, Panthenol, Cucumber Extract. Sodium PCA Phenoxyet hanol. Citr ic Acid, Licorice Extract (Giycyrrhiza Glabra Root Extract). Calendula Extract (Calendula Offici nalis Flower Extract) , Shea Butter (Butyrospermum Parkii Butter) , Jojoba Oil (Simmondsia Chinensis Seed O il), Vitamin B3 (Niacinamide), Sodium Hyaluronate (Hyaluronic Acid)